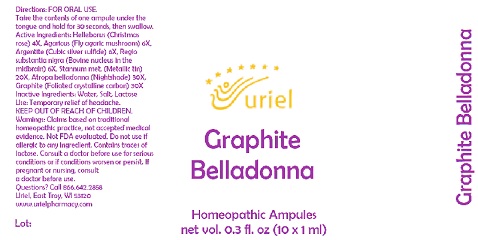 DRUG LABEL: Graphite Belladonna
NDC: 48951-5126 | Form: LIQUID
Manufacturer: Uriel Pharmacy, Inc.
Category: homeopathic | Type: HUMAN OTC DRUG LABEL
Date: 20211025

ACTIVE INGREDIENTS: AMANITA MUSCARIA FRUITING BODY 6 [hp_X]/1 mL; TIN 20 [hp_X]/1 mL; BOS TAURUS BRAIN 6 [hp_X]/1 mL; HELLEBORUS NIGER ROOT 4 [hp_X]/1 mL; ATROPA BELLADONNA 30 [hp_X]/1 mL; GRAPHITE 30 [hp_X]/1 mL; SILVER SULFIDE 6 [hp_X]/1 mL
INACTIVE INGREDIENTS: SODIUM CHLORIDE; LACTOSE, UNSPECIFIED FORM; WATER

Graphite Belladonna

INDICATIONS AND USAGE

Directions: FOR ORAL USE.

DOSAGE AND ADMINISTRATION

Take the contents of one ampule under the tongue and hold for 30 seconds, then swallow.

ACTIVE INGREDIENT

Active Ingredients: Helleborus (Christmas rose) 4X, Agaricus (Fly agaric mushroom) 6X, Argentite (Cubic silver sulfide) 6X,
Regio substantia nigra (Bovine nucleus in the midbrain) 6X, Stannum met. (Metallic tin) 20X, Atropa belladonna (Nightshade) 30X,
Graphite (Foliated crystalline carbon) 30X

Inactive Ingredients: Water, Salt, Lactose

PURPOSE

Use: Temporary relief of headache.

KEEP OUT OF REACH OF CHILDREN.

WARNINGS

Warnings: Claims based on traditional homeopathic practice, not accepted medical evidence. Not FDA evaluated. Do not use if allergic to any ingredient. Contains traces of lactose. Consult a doctor before use for serious conditions or if conditions worsen or persist. If pregnant or nursing, consult a doctor before use.

Questions? Call 866.642.2858
Uriel, East Troy, WI 53120
www.urielpharmacy.com Lot: